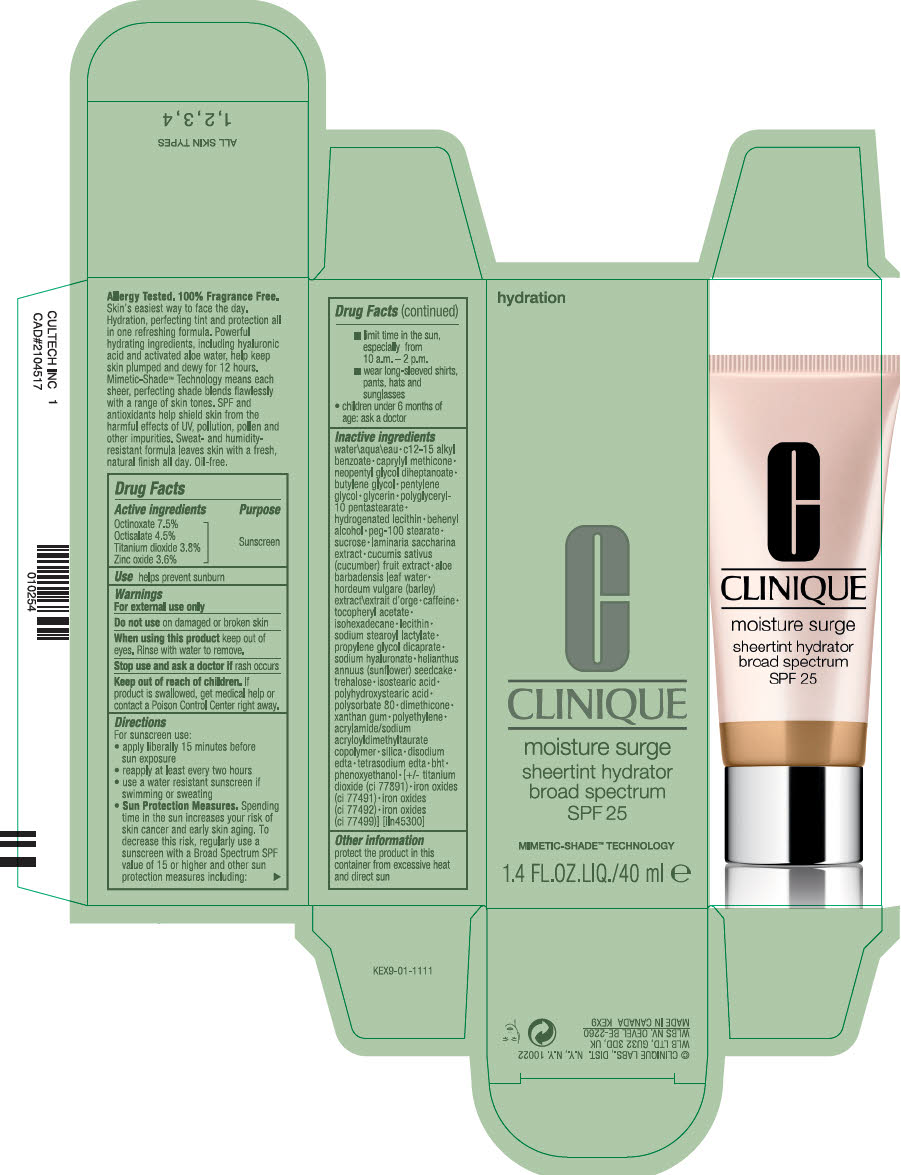 DRUG LABEL: MOISTURE SURGE SHEERTINT HYDRATOR BROAD SPECTRUM SPF 25
NDC: 49527-074 | Form: CREAM
Manufacturer: CLINIQUE LABORATORIES LLC
Category: otc | Type: HUMAN OTC DRUG LABEL
Date: 20231013

ACTIVE INGREDIENTS: OCTINOXATE 75 mg/1 mL; OCTISALATE 45 mg/1 mL; TITANIUM DIOXIDE 38 mg/1 mL; ZINC OXIDE 36 mg/1 mL
INACTIVE INGREDIENTS: PENTYLENE GLYCOL; GLYCERIN; POLYGLYCERYL-10 PENTASTEARATE; HYDROGENATED SOYBEAN LECITHIN; DOCOSANOL; PEG-100 STEARATE; SUCROSE; SACCHARINA LATISSIMA; CUCUMBER; ALOE VERA LEAF; BARLEY; CAFFEINE; .ALPHA.-TOCOPHEROL ACETATE; ISOHEXADECANE; SODIUM STEAROYL LACTYLATE; PROPYLENE GLYCOL DICAPRATE; HYALURONATE SODIUM; BUTYLENE GLYCOL; HELIANTHUS ANNUUS SEEDCAKE; TREHALOSE; ISOSTEARIC ACID; POLYSORBATE 80; DIMETHICONE; XANTHAN GUM; HIGH DENSITY POLYETHYLENE; SILICON DIOXIDE; EDETATE DISODIUM ANHYDROUS; EDETATE SODIUM; BUTYLATED HYDROXYTOLUENE; PHENOXYETHANOL; FERRIC OXIDE RED; FERRIC OXIDE YELLOW; FERROSOFERRIC OXIDE; WATER; ALKYL (C12-15) BENZOATE; CAPRYLYL TRISILOXANE; NEOPENTYL GLYCOL DIHEPTANOATE

MOISTURE SURGE SHEERTINT HYDRATOR BROAD SPECTRUM SPF 25

Drug Facts

Active ingredients

Octinoxate 7.5%
Octisalate 4.5%
Titanium dioxide 3.8%
Zinc oxide 3.6%

Purpose

Sunscreen

Use

helps prevent sunburn

Warnings

For external use only

Do not use on damaged or broken skin

When using this product keep out of eyes. Rinse with water to remove.

Stop use and ask a doctor if rash occurs

Keep out of reach of children. If product is swallowed, get medical help or contact a Poison Control Center right away.

Directions

For sunscreen use:

- apply liberally 15 minutes before sun exposure
- reapply at least every two hours
- use a water resistant sunscreen if swimming or sweating
- Sun Protection Measures. Spending time in the sun increases your risk of skin cancer and early skin aging. To decrease this risk, regularly use a sunscreen with a Broad Spectrum SPF value of 15 or higher and other sun protection measures including:
  - limit time in the sun, especially from 10 a.m. – 2 p.m.
  - wear long-sleeved shirts, pants, hats and sunglasses
- children under 6 months of age: ask a doctor

Inactive ingredients

water\aqua\eau • c12-15 alkyl benzoate • caprylyl methicone • neopentyl glycol diheptanoate • butylene glycol • pentylene glycol • glycerin • polyglyceryl-10 pentastearate • hydrogenated lecithin • behenyl alcohol • peg-100 stearate • sucrose • laminaria saccharina extract • cucumis sativus (cucumber) fruit extract • aloe barbadensis leaf water • hordeum vulgare (barley) extract\extrait d'orge • caffeine • tocopheryl acetate • isohexadecane • lecithin • sodium stearoyl lactylate • propylene glycol dicaprate • sodium hyaluronate • helianthus annuus (sunflower) seedcake • trehalose • isostearic acid • polyhydroxystearic acid • polysorbate 80 • dimethicone • xanthan gum • polyethylene • acrylamide/sodium acryloyldimethyltaurate copolymer • silica • disodium edta • tetrasodium edta • bht • phenoxyethanol • [+/- titanium dioxide (ci 77891) • iron oxides (ci 77491) • iron oxides (ci 77492) • iron oxides (ci 77499)] [iln45300]

Other information

protect the product in this container from excessive heat and direct sun

PRINCIPAL DISPLAY PANEL - 40 ml Tube Carton

hydration

CLINIQUE

moisture surge

sheertint hydrator
broad spectrum
SPF 25

MIMETIC-SHADE™ TECHNOLOGY

1.4 FL.OZ.LIQ./40 ml e